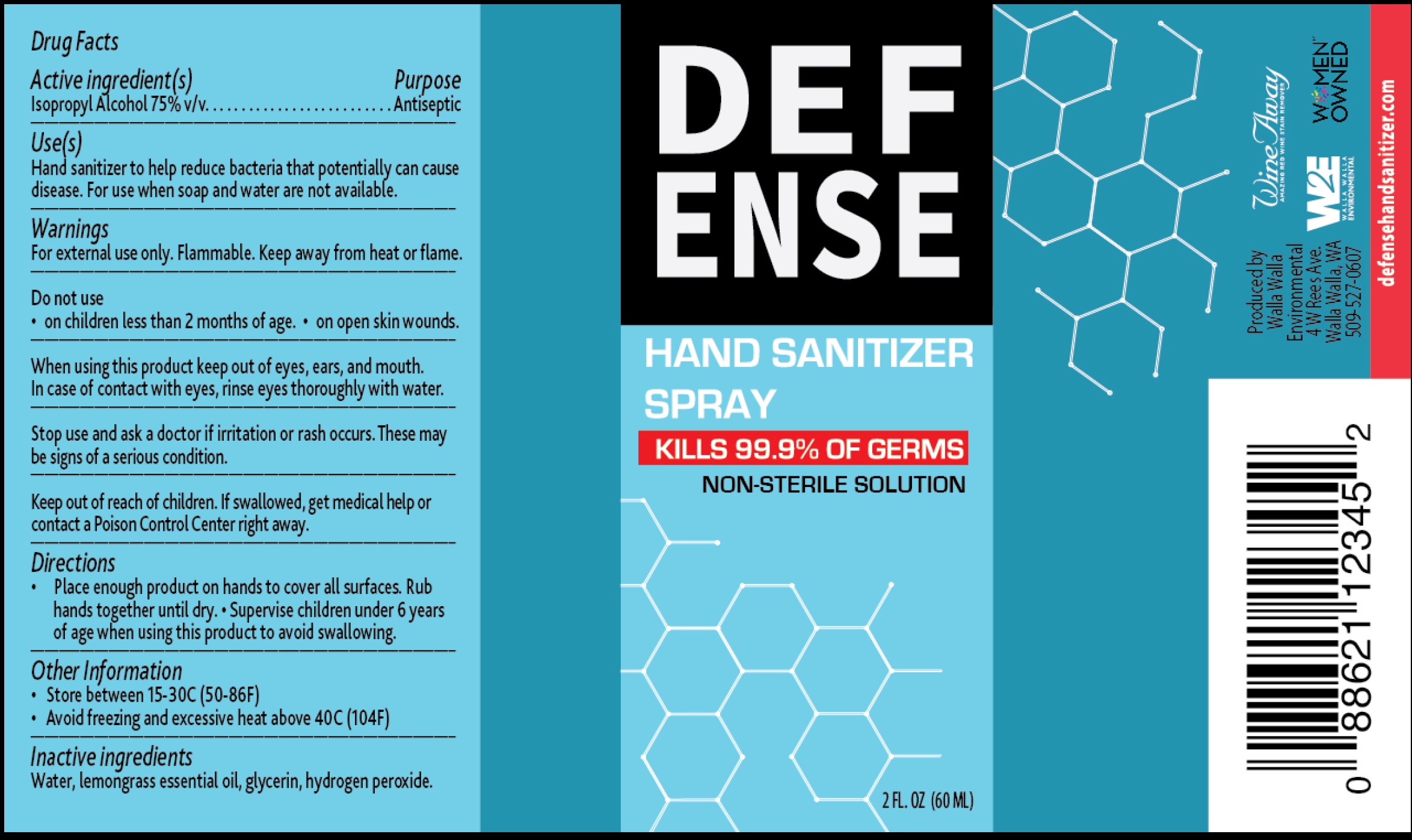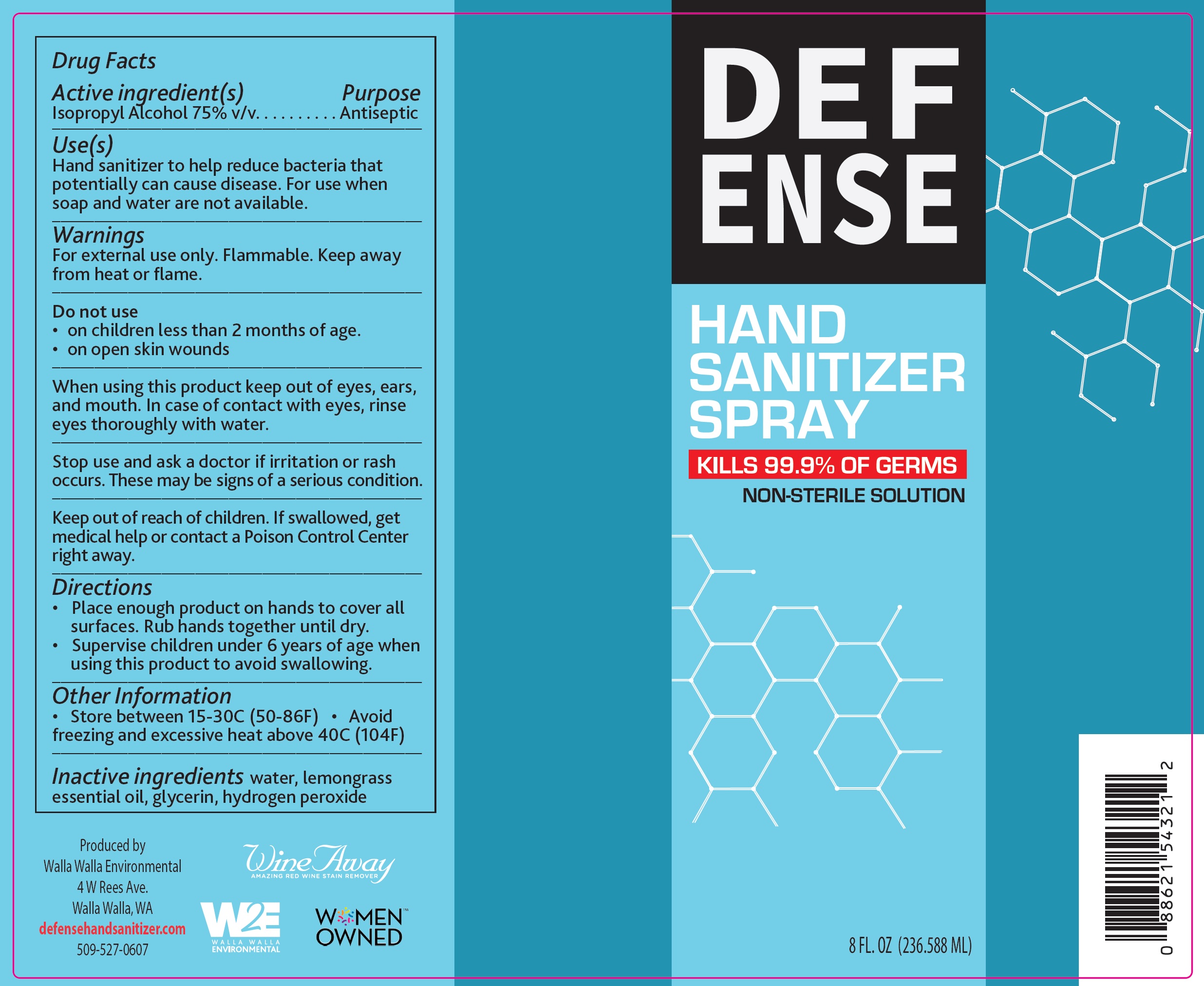 DRUG LABEL: DEFENSE Hand Sanitizer
NDC: 80579-000 | Form: LIQUID
Manufacturer: Walla Walla Environmental, Inc.
Category: otc | Type: HUMAN OTC DRUG LABEL
Date: 20220831

ACTIVE INGREDIENTS: ISOPROPYL ALCOHOL 0.75 mL/1 mL
INACTIVE INGREDIENTS: WATER; WEST INDIAN LEMONGRASS OIL; GLYCERIN; HYDROGEN PEROXIDE

DEFENSE Hand Sanitizer Spray

Active ingredient(s)

Isopropyl Alcohol 75% v/v

Purpose

Antiseptic

Use(s)

Hand sanitizer to help reduce bacteria that potentially can cause disease. For use when soap and water are not available.

Warnings

For external use only. Flammable. Keep away from heat or flame.

Do not use

- on children less than 2 months of age.
- on open skin wounds

When using this product

keep out of eyes, ears, and mouth. In case of contact with eyes, rinse eyes thoroughly with water.

Stop use and ask a doctor

if irritation or rash occurs. These may be signs of a serious condition.

Keep out of reach of children.

If swallowed, get medical help or contact a Poison Control Center right away.

Directions

• Place enough product on hands to cover all surfaces. Rub hands together until dry.
• Supervise children under 6 years of age when using this product to avoid swallowing.

Other Information

- Store between 15-30C (50-86F)
- Avoid freezing and excessive heat above 40C (104F)

Inactive ingredients

water, lemongrass essential oil, glycerin, hydrogen peroxide